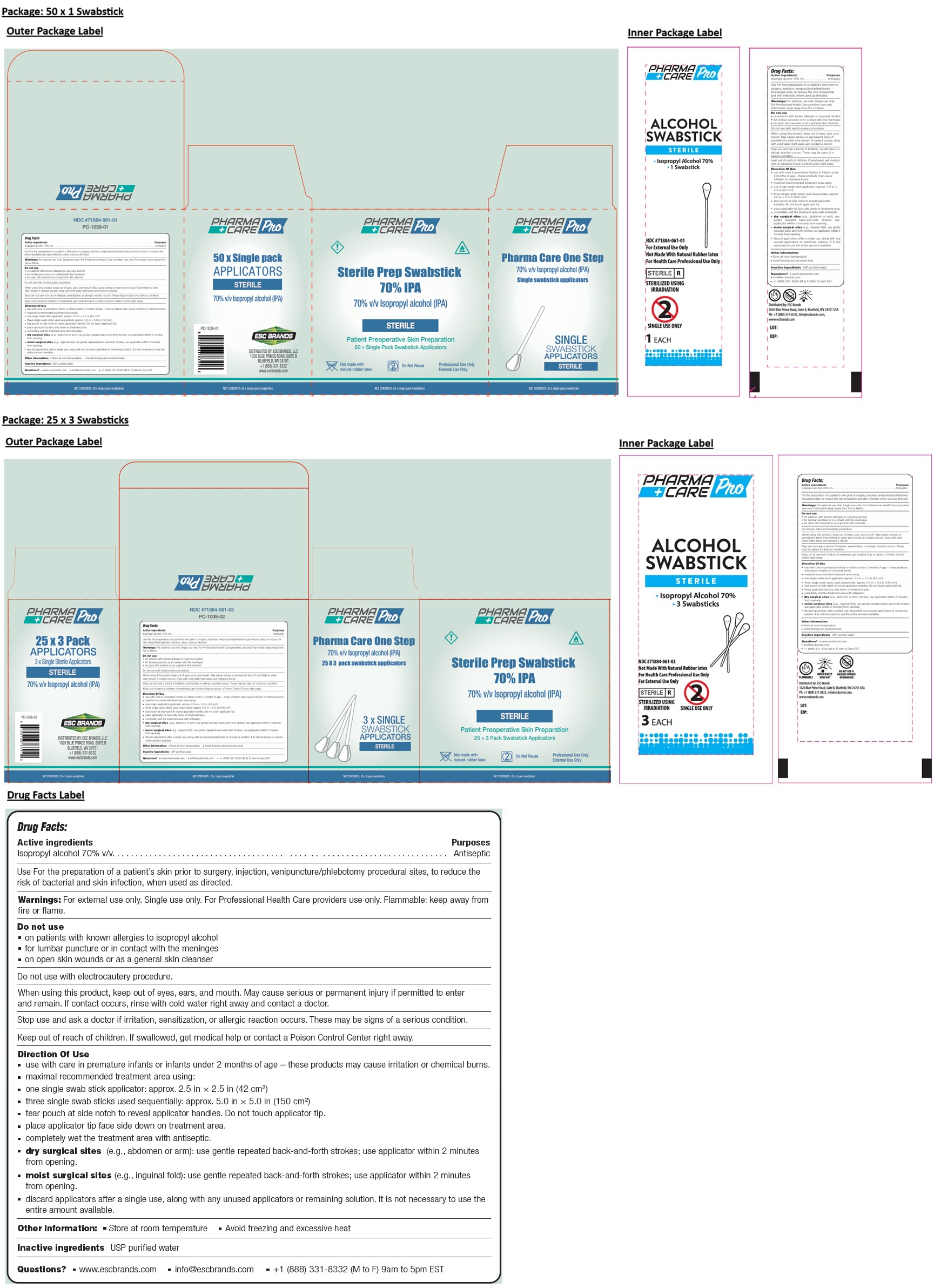 DRUG LABEL: PHARMA CARE Pro Sterile Prep Swabstick 70% IPA
NDC: 71884-061 | Form: SWAB
Manufacturer: Enviro Specialty Chemicals Inc
Category: otc | Type: HUMAN OTC DRUG LABEL
Date: 20251210

ACTIVE INGREDIENTS: ISOPROPYL ALCOHOL 70 mL/100 mL
INACTIVE INGREDIENTS: WATER

PHARMA CARE Pro Sterile Prep Swabstick 70% IPA

Active ingredients

Isopropyl alcohol 70% v/v

Purposes

Antiseptic

Use

For the preparation of a patient’s skin prior to surgery, injection, venipuncture/phlebotomy procedural sites, to reduce the risk of bacterial and skin infection, when used as directed.

Warnings:

For external use only. Single use only. For Professional Health Care providers use only. Flammable: keep away from fire or flame.

Do not use
• on patients with known allergies to isopropyl alcohol
• for lumbar puncture or in contact with the meninges
• on open skin wounds or as a general skin cleanser

Do not use with electrocautery procedure.

When using this product, keep out of eyes, ears, and mouth. May cause serious or permanent injury if permitted to enter and remain. If contact occurs, rinse with cold water right away and contact a doctor.

Stop use and ask a doctor if irritation, sensitization, or allergic reaction occurs. These may be signs of a serious condition.

Keep out of reach of children. If swallowed, get medical help or contact a Poison Control Center right away.

Direction Of Use

• use with care in premature infants or infants under 2 months of age – these products may cause irritation or chemical burns.
• maximal recommended treatment area using:
• one single swab stick applicator: approx. 2.5 in × 2.5 in (42 cm²)
• three single swab sticks used sequentially: approx. 5.0 in × 5.0 in (150 cm²)
• tear pouch at side notch to reveal applicator handles. Do not touch applicator tip.
• place applicator tip face side down on treatment area.
• completely wet the treatment area with antiseptic
• dry surgical sites (e.g., abdomen or arm): use gentle repeated back-and-forth strokes; use applicator within 2 minutes from opening.
• moist surgical sites (e.g., inguinal fold): use gentle repeated back-and-forth strokes; use applicator within 2 minutes from opening.
• discard applicators after a single use, along with any unused applicators or remaining solution. It is not necessary to use the entire amount available.

Other information:

• Store at room temperature • Avoid freezing and excessive heat

Inactive ingredients

USP purified water

Questions?

• www.escbrands.com • info@escbrands.com • +1 (888) 331-8332 (M to F) 9am to 5pm EST

Patient Preoperative Skin Preparation

Not made with natural rubber latex

Do Not Reuse

Professional Use Only
External Use Only

Pharma Care One Step

Single swab stick applicators

DISTRIBUTED BY: ESC BRANDS, LLC
1026 BLUE PRINCE ROAD, SUITE B
BLUEFIELD, WV 24701 USA

ALCOHOL
SWABSTICK

STERILIZED USING IRRADIATION

SINGLE USE ONLY

FLAMMABLE

AVOID DIRECT SUNLIGHT

DO NOT USE IF PACKAGE OPENED OR DAMAGED